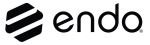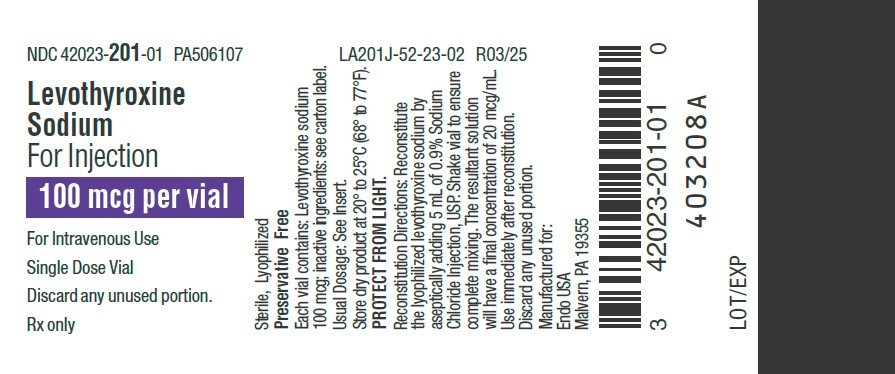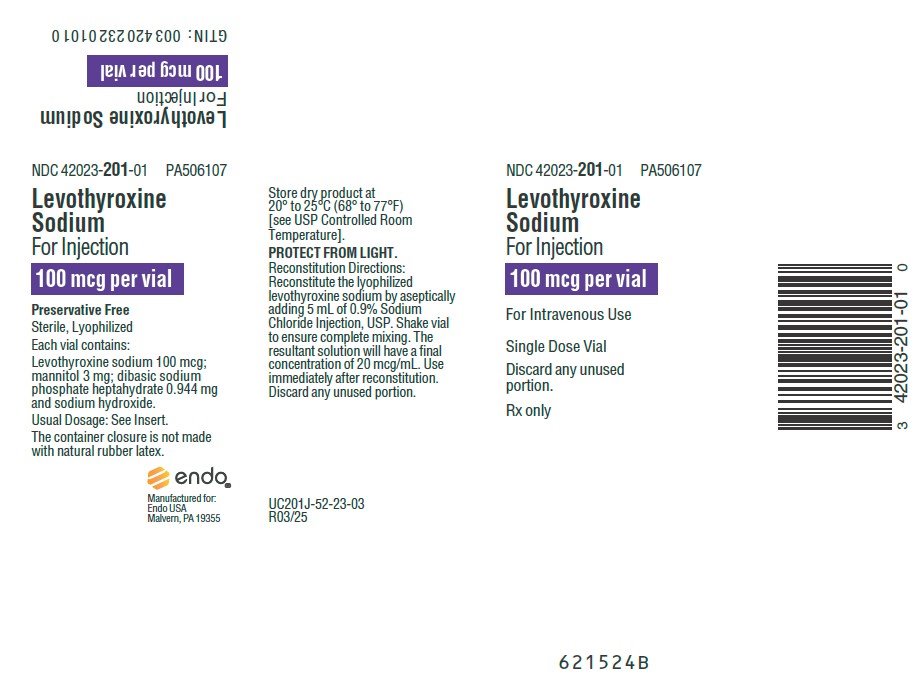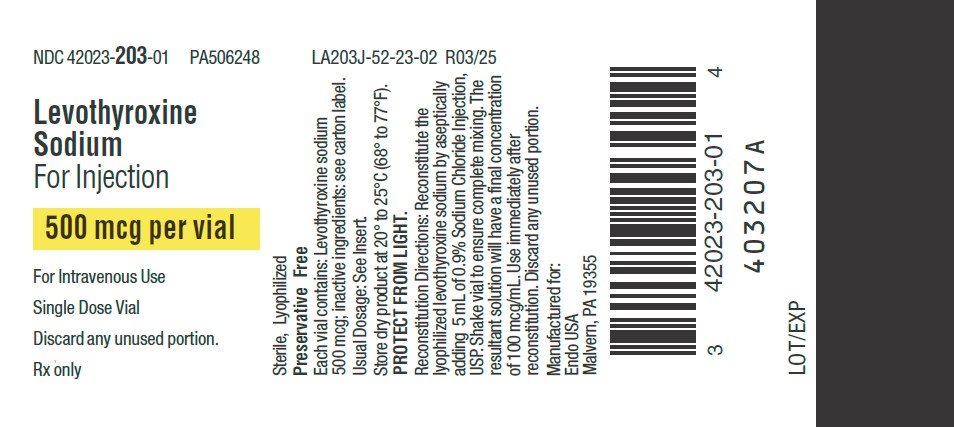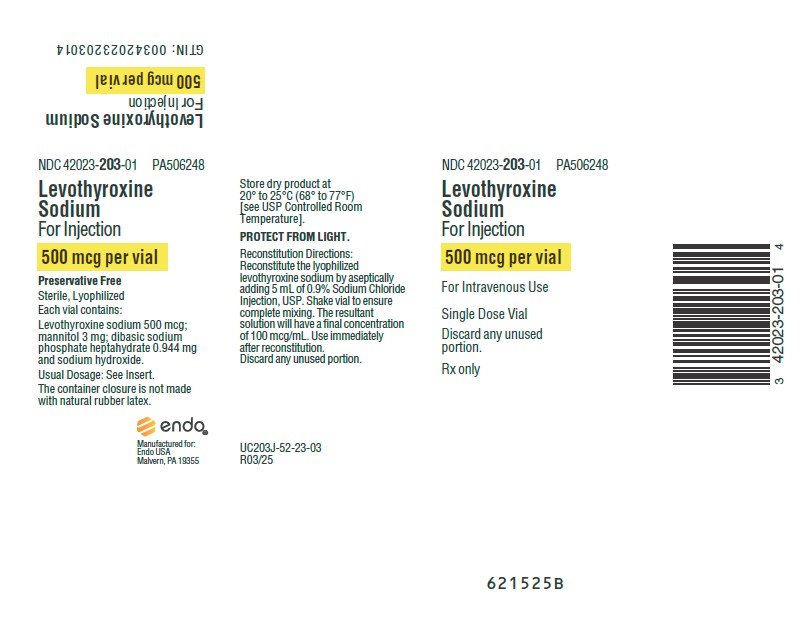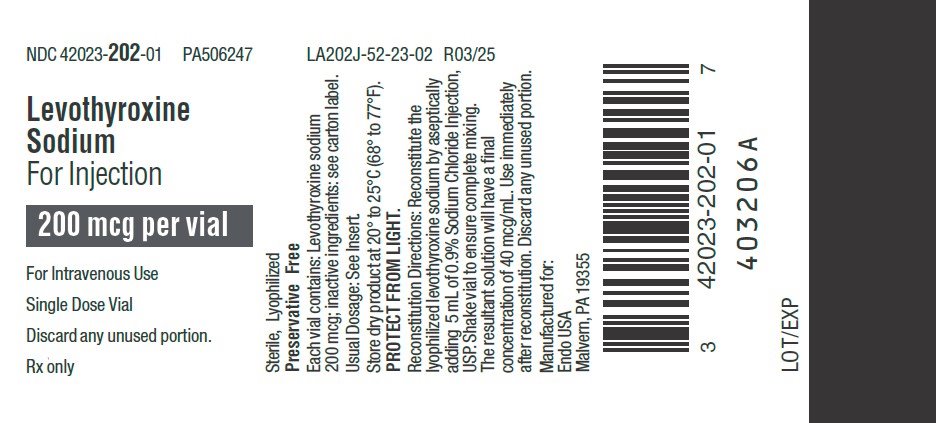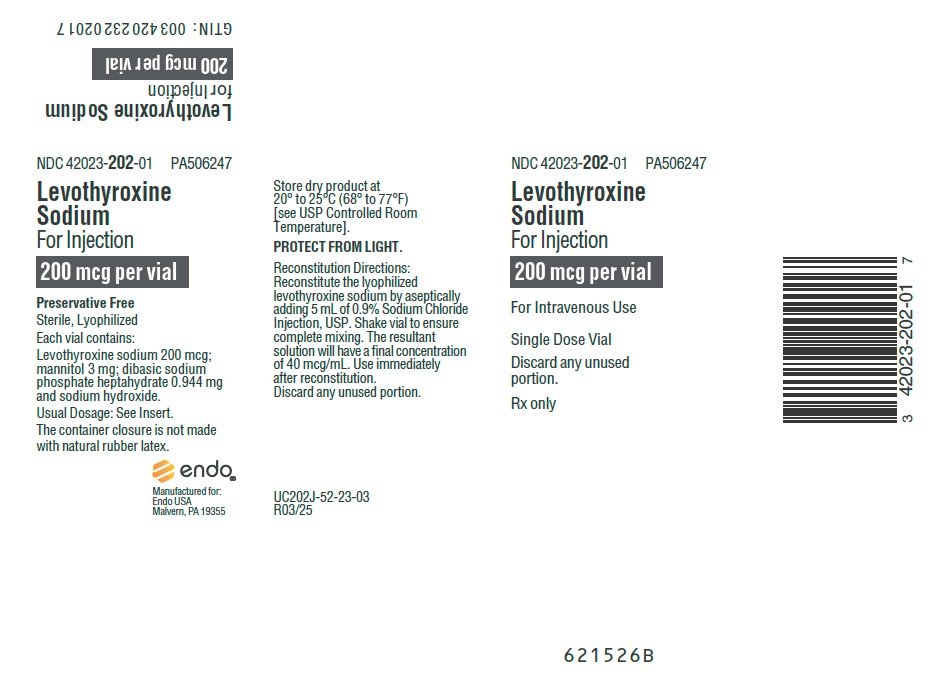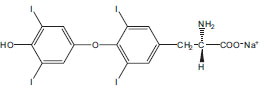 DRUG LABEL: Levothyroxine Sodium
NDC: 42023-202 | Form: INJECTION, POWDER, LYOPHILIZED, FOR SOLUTION
Manufacturer: ENDO USA, Inc.
Category: prescription | Type: HUMAN PRESCRIPTION DRUG LABEL
Date: 20250428

ACTIVE INGREDIENTS: LEVOTHYROXINE SODIUM ANHYDROUS 200 ug/5 mL
INACTIVE INGREDIENTS: MANNITOL; SODIUM PHOSPHATE, DIBASIC, HEPTAHYDRATE; SODIUM HYDROXIDE

HIGHLIGHTS OF PRESCRIBING INFORMATION

These highlights do not include all the information needed to use Levothyroxine Sodium for Injection safely and effectively. See full prescribing information for Levothyroxine Sodium for Injection.
Levothyroxine Sodium for Injection
Initial U.S. Approval: 1969

WARNING: NOT FOR TREATMENT OF OBESITY OR FOR WEIGHT LOSS

Thyroid hormones, including Levothyroxine Sodium for Injection, should not be used for the treatment of obesity or for weight loss. (5.3)
Larger doses may produce serious or even life threatening manifestations of toxicity. (6)

1 INDICATIONS AND USAGE

Levothyroxine Sodium is an L-thyroxine product. Levothyroxine (T4) Sodium for Injection is indicated for the treatment of myxedema coma. (1)

Important Limitations of Use:

The relative bioavailability of this drug has not been established. Use caution when converting patients from oral to intravenous levothyroxine.

2 DOSAGE AND ADMINISTRATION

- An initial intravenous loading dose of Levothyroxine Sodium for Injection between 300 to 500 mcg followed by once daily intravenous maintenance doses between 50 and 100 mcg should be administered, as clinically indicated, until the patient can tolerate oral therapy. (2.1)
- Reconstitute the lyophilized Levothyroxine Sodium for Injection by aseptically adding 5 mL of 0.9% Sodium Chloride Injection, USP. Shake vial to ensure complete mixing. Reconstituted drug product is preservative free. Use immediately after reconstitution. Discard any unused portion. (2.3)
- Do not add to other IV fluids. (2.3)

3 DOSAGE FORMS AND STRENGTHS

Lyophilized powder for injection in single dose vials: 100 mcg, 200 mcg and 500 mcg. (3)

4 CONTRAINDICATIONS

None.

5 WARNINGS AND PRECAUTIONS

- Excessive bolus doses of Levothyroxine Sodium for Injection (> 500 mcg) are associated with cardiac complications, particularly in the elderly and in patients with an underlying cardiac condition. Initiate therapy with doses at the lower end of the recommended range. (5.1)
- Close observation of the patient following the administration of Levothyroxine Sodium for Injection is advised. (5.1)
- Levothyroxine Sodium for Injection therapy for patients with previously undiagnosed endocrine disorders, including adrenal insufficiency, hypopituitarism, and diabetes insipidus, may worsen symptoms of these endocrinopathies. (5.2)

6 ADVERSE REACTIONS

Excessive doses of L-thyroxine can predispose to signs and symptoms compatible with hyperthyroidism. (6)

To report SUSPECTED ADVERSE REACTIONS, contact Fresenius Kabi USA, LLC at 1-800-551-7176 or FDA at 1-800-FDA-1088 or www.fda.gov/medwatch.

7 DRUG INTERACTIONS

Many drugs affect thyroid hormone pharmacokinetics and metabolism (e.g., absorption, synthesis, secretion, catabolism, protein binding, and target tissue response) and may alter the therapeutic response to Levothyroxine Sodium for Injection. (7, 12.3)

8 USE IN SPECIFIC POPULATIONS

Elderly and those with underlying cardiovascular disease should receive doses at the lower end of the recommended range. (8.5)

FULL PRESCRIBING INFORMATION

WARNING: NOT FOR TREATMENT OF OBESITY OR FOR WEIGHT LOSS

Thyroid hormones, including Levothyroxine Sodium for Injection, should not be used for the treatment of obesity or for weight loss. (5.3)
Larger doses may produce serious or even life threatening manifestations of toxicity. (6)

1 INDICATIONS AND USAGE

Levothyroxine Sodium for Injection is indicated for the treatment of myxedema coma. Important Limitations of Use: The relative bioavailability between Levothyroxine Sodium for Injection and oral levothyroxine products has not been established. Caution should be used when switching patients from oral levothyroxine products to Levothyroxine Sodium for Injection as accurate dosing conversion has not been studied.

2 DOSAGE AND ADMINISTRATION

2.1 Dosage

An initial intravenous loading dose of Levothyroxine Sodium for Injection between 300 to 500 mcg, followed by once daily intravenous maintenance doses between 50 and 100 mcg, should be administered, as clinically indicated, until the patient can tolerate oral therapy. The age, general physical condition, cardiac risk factors, and clinical severity of myxedema and duration of myxedema symptoms should be considered when determining the starting and maintenance dosages of Levothyroxine Sodium for Injection.

Levothyroxine Sodium for Injection produces a gradual increase in the circulating concentrations of the hormone with an approximate half-life of 9 to 10 days in hypothyroid patients. Daily administration of Levothyroxine Sodium for Injection should be maintained until the patient is capable of tolerating an oral dose and is clinically stable. For chronic treatment of hypothyroidism, an oral dosage form of levothyroxine should be used to maintain a euthyroid state. Relative bioavailability between Levothyroxine Sodium for Injection and oral levothyroxine products has not been established. Based on medical practice, the relative bioavailability between oral and intravenous administration of Levothyroxine Sodium for Injection is estimated to be from 48 to 74%. Due to differences in absorption characteristics of patients and the oral levothyroxine product formulations, TSH and thyroid hormone levels should be measured a few weeks after initiating oral levothyroxine and dose adjusted accordingly.

2.2 Dosing in the Elderly and in Patients with Cardiovascular Disease

Intravenous levothyroxine may be associated with cardiac toxicity–including arrhythmias, tachycardia, myocardial ischemia and infarction, or worsening of congestive heart failure and death–in the elderly and in those with underlying cardiovascular disease. Therefore, cautious use, including doses in the lower end of the recommended range, may be warranted in these populations.

2.3 Reconstitution Directions

Reconstitute the lyophilized Levothyroxine Sodium for Injection by aseptically adding 5 mL of 0.9% Sodium Chloride Injection, USP only. Shake vial to ensure complete mixing. The resultant solution will have a final concentration of approximately 20 mcg per mL, 40 mcg per mL and 100 mcg per mL for the 100 mcg, 200 mcg and 500 mcg vials, respectively. Reconstituted drug product is preservative free and is stable for 4 hours. Discard any unused portion. DO NOT ADD LEVOTHYROXINE SODIUM FOR INJECTION TO OTHER IV FLUIDS. Parenteral drug products should be inspected visually for particulate matter and discoloration prior to administration, whenever solution and container permit.

3 DOSAGE FORMS AND STRENGTHS

Levothyroxine Sodium for Injection is supplied as a lyophilized powder at three strengths in single dose amber-colored vials: 100 mcg, 200 mcg and 500 mcg.

4 CONTRAINDICATIONS

None.

5 WARNINGS AND PRECAUTIONS

5.1 Risk of Cardiac Complications in Elderly and in Patients with Cardiovascular Disease

Excessive bolus dosing of Levothyroxine Sodium for Injection (greater than 500 mcg) are associated with cardiac complications, particularly in the elderly and in patients with an underlying cardiac condition. Adverse events that can potentially be related to the administration of large doses of Levothyroxine Sodium for Injection include arrhythmias, tachycardia, myocardial ischemia and infarction, or worsening of congestive heart failure and death. Cautious use, including doses in the lower end of the recommended range, may be warranted in these populations. Close observation of the patient following the administration of Levothyroxine Sodium for Injection is advised.

5.2 Need for Concomitant Glucocorticoids and Monitoring for Other Diseases in Patients with Endocrine Disorders

Occasionally, chronic autoimmune thyroiditis, which can lead to myxedema coma, may occur in association with other autoimmune disorders such as adrenal insufficiency, pernicious anemia, and insulin‑dependent diabetes mellitus. Patients should be treated with replacement glucocorticoids prior to initiation of treatment with Levothyroxine Sodium for Injection, until adrenal function has been adequately assessed. Failure to do so may precipitate an acute adrenal crisis when thyroid hormone therapy is initiated, due to increased metabolic clearance of glucocorticoids by thyroid hormone. With initiation of Levothyroxine Sodium for Injection, patients with myxedema coma should also be monitored for previously undiagnosed diabetes insipidus.

5.3 Not Indicated for Treatment of Obesity

Thyroid hormones, including Levothyroxine Sodium for Injection, either alone or with other therapeutic agents, should not be used for the treatment of obesity or for weight loss. In euthyroid patients, doses within the range of daily hormonal requirements are ineffective for weight reduction. Larger doses may produce serious or even life threatening manifestations of toxicity, particularly when given in association with sympathomimetic amines such as those used for their anorectic effects [see Adverse Reactions (6) and Overdosage (10)].

6 ADVERSE REACTIONS

ExcessI doses of levothyroxine can predispose to signs and symptoms compatible with hyperthyroidism. The signs and symptoms of thyrotoxicosis include, but are not limited to: exophthalmic goiter, weight loss, increased appetite, palpitations, nervousness, diarrhea, abdominal cramps, sweating, tachycardia, increased pulse and blood pressure, cardiac arrhythmias, angina pectoris, tremors, insomnia, heat intolerance, fever, and menstrual irregularities.

7 DRUG INTERACTIONS

Many drugs affect thyroid hormone pharmacokinetics and metabolism (e.g., synthesis, secretion, catabolism, protein binding, and target tissue response) and may alter the therapeutic response to Levothyroxine Sodium for Injection. In addition, thyroid hormones and thyroid status have varied effects on the pharmacokinetics and actions of other drugs (see Section 12.3).

7.1 Antidiabetic Therapy

Addition of levothyroxine to antidiabetic or insulin therapy may result in increased antidiabetic agent or insulin requirements. Careful monitoring of diabetic control is recommended, especially when thyroid therapy is started, changed, or discontinued.

7.2 Oral Anticoagulants

Levothyroxine increases the response to oral anticoagulant therapy. Therefore, a decrease in the dose of anticoagulant may be warranted with correction of the hypothyroid state or when the Levothyroxine Sodium for Injection dose is increased. Prothrombin time should be closely monitored to permit appropriate and timely dosage adjustments.

7.3 Digitalis Glycosides

The therapeutic effects of digitalis glycosides may be reduced by levothyroxine. Serum digitalis glycoside levels may be decreased when a hypothyroid patient becomes euthyroid, necessitating an increase in the dose of digitalis glycosides.

7.4 Antidepressant Therapy

Concurrent use of tricyclic (e.g., amitriptyline) or tetracyclic (e.g., maprotiline) antidepressants and levothyroxine may increase the therapeutic and toxic effects of both drugs, possibly due to increased receptor sensitivity to catecholamines. Toxic effects may include increased risk of cardiac arrhythmias and CNS stimulation; onset of action of tricyclics may be accelerated. Administration of sertraline in patients stabilized on levothyroxine may result in increased levothyroxine requirements.

7.5 Ketamine

Concurrent use may produce marked hypertension and tachycardia; cautious administration to patients receiving thyroid hormone therapy is recommended.

7.6 Sympathomimetics

Concurrent use may increase the effects of sympathomimetics or thyroid hormone. Thyroid hormones may increase the risk of coronary insufficiency when sympathomimetic agents are administered to patients with coronary artery disease.

7.7 Drug-Laboratory Test Interactions

Changes in thyroxine binding globulin (TBG) concentration must be considered when interpreting levothyroxine and triiodothyronine values, which necessitates measurement and evaluation of unbound (free) hormone and/or determination of the free levothyroxine index. Pregnancy, infectious hepatitis, estrogens, estrogen containing oral contraceptives, and acute intermittent porphyria increase TBG concentrations. Decreases in TBG concentrations are observed in nephrosis, severe hypoproteinemia, severe liver disease, acromegaly, and after androgen or corticosteroid therapy. Familial hyper or hypo thyroxine binding globulinemias have been described, with the incidence of TBG deficiency approximating 1 in 9000.

8 USE IN SPECIFIC POPULATIONS

8.1 Pregnancy

Pregnancy Category A – There are no reported cases of Levothyroxine Sodium for Injection used to treat myxedema coma in patients who were pregnant or lactating. Studies in pregnant women treated with oral levothyroxine to maintain a euthyroid state have not shown an increased risk of fetal abnormalities. Therefore, pregnant patients who develop myxedema should be treated with Levothyroxine Sodium for Injection as the risk of nontreatment is associated with a high probability of significant morbidity or mortality to the maternal patient and the fetus.

8.2 Labor and Delivery

Patients in labor who develop myxedema have not been reported in the literature. However, patients should be treated with Levothyroxine Sodium for Injection as the risk of nontreatment is associated with a high probability of significant morbidity or mortality to the maternal patient and the fetus.

8.3 Nursing Mothers

Adequate replacement doses of thyroid hormones are required to maintain normal lactation. There are no reported cases of Levothyroxine Sodium for Injection used to treat myxedema coma in patients who are lactating. However, such patients should be treated with Levothyroxine Sodium for Injection as the risk of nontreatment is associated with a high probability of significant morbidity or mortality to the nursing patient.

8.4 Pediatric Use

Myxedema coma is a disease of the elderly. An approved, oral dosage form of levothyroxine should be used in the pediatric patient population for maintaining a euthyroid state in non-complicated hypothyroidism.

8.5 Geriatric Use and Patients with Underlying Cardiovascular Disease

See Section 2, Dosage and Administration, for full prescribing information in the geriatric patient population. Because of the increased prevalence of cardiovascular disease in the elderly, cautious use of Levothyroxine Sodium for Injection in the elderly and in patients with known cardiac risk factors is advised. Atrial fibrillation is a common side effect associated with levothyroxine treatment in the elderly [see Dosage and Administration (2) and Warnings and Precautions (5)].

10 OVERDOSAGE

In general, the signs and symptoms of overdosage with levothyroxine are those of hyperthyroidism [see Warnings and Precautions (5) and Adverse Reactions (6)]. In addition, confusion and disorientation may occur. Cerebral embolism, shock, coma, and death have been reported. Excessive doses of Levothyroxine Sodium for Injection (greater than 500 mcg) are associated with cardiac complications in patients with underlying cardiac disease.

Treatment of Overdosage

Levothyroxine Sodium for Injection should be reduced in dose or temporarily discontinued if signs or symptoms of overdosage occur. To obtain up-to-date information about the treatment of overdose, a good resource is the certified Regional Poison Control Center. In managing overdosage, consider the possibility of multiple drug overdoses, interaction among drugs, and unusual drug kinetics in the patient.

In the event of an overdose, appropriate supportive treatment should be initiated as dictated by the patient’s medical status.

11 DESCRIPTION

Levothyroxine Sodium for Injection contains synthetic crystalline levothyroxine (L-thyroxine) sodium salt. Levothyroxine sodium has an empirical formula of C15H10I4NNaO4, a molecular weight of 798.85 g/mol (anhydrous), and the following structural formula:

Levothyroxine Sodium for Injection is a sterile, preservative-free lyophilized powder consisting of the active ingredient, levothyroxine sodium, and the excipients dibasic sodium phosphate heptahydrate, USP; mannitol, USP; and sodium hydroxide, NF in single dose amber glass vials. Levothyroxine Sodium for Injection is available at three dosage strengths: 100 mcg per vial, 200 mcg per vial and 500 mcg per vial.

12 CLINICAL PHARMACOLOGY

12.1 Mechanism of Action

Thyroid hormones exert their physiologic actions through control of DNA transcription and protein synthesis. Triiodothyronine (T3) and levothyroxine (T4) diffuse into the cell nucleus and bind to thyroid receptor proteins attached to DNA. This hormone nuclear receptor complex activates gene transcription and synthesis of messenger RNA and cytoplasmic proteins.

The physiological actions of thyroid hormones are produced predominantly by T3, the majority of which (approximately 80%) is derived from T4 by deiodination in peripheral tissues.

12.2 Pharmacodynamics

Thyroid hormone synthesis and secretion is regulated by the hypothalamic pituitary-thyroid axis. Thyrotropin releasing hormone (TRH) released from the hypothalamus stimulates secretion of thyrotropin stimulating hormone (TSH) from the anterior pituitary. TSH, in turn, is the physiologic stimulus for the synthesis and secretion of thyroid hormones, T4 and T3, by the thyroid gland. Circulating serum T3 and T4 levels exert a feedback effect on both TRH and TSH secretion. When serum T3 and T4 levels increase, TRH and TSH secretion decrease. When thyroid hormone levels decrease, TRH and TSH secretion increases. TSH is used for the diagnosis of hypothyroidism and evaluation of levothyroxine therapy adequacy with other laboratory and clinical data [see Dosage (2.1)]. There are drugs known to affect thyroid hormones and TSH by various mechanisms and those examples are diazepam, ethionamide, lovastatin, metoclopramide, 6-mercaptopurine, nitroprusside, perphenazine, and thiazide diuretics. Some drugs may cause a transient decrease in TSH secretion without hypothyroidism and those drugs (dose) are dopamine (greater than 1 mcg per kg per min), glucocorticoids (hydrocortisone greater than 100 mg per day or equivalent) and octreotide (greater than 100 mcg per day).

Thyroid hormones regulate multiple metabolic processes and play an essential role in normal growth and development, and normal maturation of the central nervous system and bone. The metabolic actions of thyroid hormones include augmentation of cellular respiration and thermogenesis, as well as metabolism of proteins, carbohydrates and lipids. The protein anabolic effects of thyroid hormones are essential to normal growth and development.

12.3 Pharmacokinetics

Absorption – Levothyroxine Sodium for Injection is administered via the intravenous route. Following administration, the synthetic levothyroxine cannot be distinguished from the natural hormone that is secreted endogenously.

Distribution – Circulating thyroid hormones are greater than 99% bound to plasma proteins, including thyroxine binding globulin (TBG), thyroxine binding prealbumin (TBPA), and albumin (TBA), whose capacities and affinities vary for each hormone. The higher affinity of both TBG and TBPA for T4 partially explains the higher serum levels, slower metabolic clearance, and longer half life of T4 compared to T3. Protein bound thyroid hormones exist in reverse equilibrium with small amounts of free hormone. Only unbound hormone is metabolically active. Many drugs and physiologic conditions affect the binding of thyroid hormones to serum proteins [see Warnings and Precautions (5) and Drug Interactions (7)]. Thyroid hormones do not readily cross the placental barrier [see Warnings and Precautions (5) and Use in Specific Populations (8)].

Metabolism – T4 is slowly eliminated. The major pathway of thyroid hormone metabolism is through sequential deiodination. Approximately eighty percent of circulating T3 is derived from peripheral T4 by monodeiodination. The liver is the major site of degradation for both T4 and T3, with T4 deiodination also occurring at a number of additional sites, including the kidney and other tissues. Approximately 80% of the daily dose of T4 is deiodinated to yield equal amounts of T3 and reverse T3 (r T3). T3 and r T3 are further deiodinated to diiodothyronine. Thyroid hormones are also metabolized via conjugation with glucuronides and sulfates and excreted directly into the bile and gut where they undergo enterohepatic recirculation.

Elimination – Thyroid hormones are primarily eliminated by the kidneys. A portion of the conjugated hormone reaches the colon unchanged, where it is hydrolyzed and eliminated in feces as the free hormones. Urinary excretion of T4 decreases with age.

Table 1: Pharmacokinetic Parameters of Thyroid Hormones in Euthyroid Patients

Hormone | Ratio in Thyroglobulin | Biologic Potency | Half-Life (Days) | Protein Binding (%) ^2
T4 | 10 to 20 | 1 | 6 to 8^1 | 99.96
T3 | 1 | 4 | ≤ 2 | 99.5

T4: Levothyroxine

T3: Liothyronine

^1 3 to 4 days in hyperthyroidism, 9 to 10 days in hypothyroidism.

^2 Includes TBG, TBPA, and TBA.

Drug Interactions

A listing of drug interaction with T4 is provided in the following tables, although it may not be comprehensive due to the introduction of new drugs that interact with the thyroidal axis or the discovery of previously unknown interactions. The prescriber should be aware of this fact and should consult appropriate reference sources (e.g., package inserts of newly approved drugs, medical literature) for additional information if a drug-drug interaction with levothyroxine is suspected.

Table 2: Drugs That May Alter T4 and T3 Serum Transport Without Affecting free T4 Concentration (Euthyroidism)

Drugs That May Increase Serum TBG Concentration | Drugs That May Decrease Serum TBG Concentration
Clofibrate Estrogen-containing oral contraceptives Estrogens (oral) Heroin/Methadone 5-Fluorouracil Mitotane Tamoxifen | Androgens/Anabolic Steroids Asparaginase Glucocorticoids Slow-Release Nicotinic Acid
Drugs That May Cause Protein-Binding Site Displacement
Potential impact: Administration of these agents with levothyroxine results in an initial transient increase in FT4. Continued administration results in a decrease in serum T4 and normal FT4 and TSH concentrations and, therefore, patients are clinically euthyroid.
Salicylates (> 2 g/day) | Salicylates inhibit binding of T4 and T3 to TBG and transthyretin. An initial increase in serum FT4 is followed by return of FT4 to normal levels with sustained therapeutic serum salicylate concentrations, although total-T4 levels may decrease by as much as 30%.
Other drugs: Furosemide (> 80 mg IV) Heparin Hydantoins Non-Steroidal Anti-inflammatory Drugs - Fenamates - Phenylbutazone

Table 3: Drugs That May Alter Hepatic Metabolism of T4 (Hypothyroidism)

Potential impact: Stimulation of hepatic microsomal drug-metabolizing enzyme activity may cause increased hepatic degradation of levothyroxine, resulting in increased levothyroxine requirements.

Drug or Drug Class
Carbamazepine Hydantoins | Phenytoin and carbamazepine reduce serum protein binding of levothyroxine, and total- and free- T4 may be reduced by 20% to 40%, but most patients have normal serum TSH levels and are clinically euthyroid.
Other drugs: Phenobarbital Rifampin

Table 4: Drugs That May Decrease Conversion of T4 to T3

Potential impact: Administration of these enzyme inhibitors decreases the peripheral conversion of T4 to T3, leading to decreased T3 levels. However, serum T4 levels are usually normal but may occasionally be slightly increased.

Drug or Drug Class | Effect
Beta-adrenergic antagonists (e.g., Propranolol > 160 mg/day) | In patients treated with large doses of propranolol (>160 mg/day), T3 and T4 levels change slightly, TSH levels remain normal, and patients are clinically euthyroid. It should be noted that actions of particular beta-adrenergic antagonists may be impaired when the hypothyroid patient is converted to the euthyroid state.
Glucocorticoids (e.g., Dexamethasone > 4 mg/day) | Short-term administration of large doses of glucocorticoids may decrease serum T3 concentrations by 30% with minimal change in serum T4 levels. However, long-term glucocorticoid therapy may result in slightly decreased T3 and T4 levels due to decreased TBG production (see above).
Other drug: Amiodarone

13 NONCLINICAL TOXICOLOGY

13.1 Carcinogenesis, Mutagenesis, Impairment of Fertility

Animal studies have not been performed to evaluate the carcinogenic potential, mutagenic potential or effects on fertility of Levothyroxine Sodium for Injection.

13.2 Animal Toxicology and Pharmacology

No animal toxicology studies have been conducted with Levothyroxine Sodium for Injection.

14 CLINICAL STUDIES

No clinical studies have been conducted with Levothyroxine Sodium for Injection in patients with myxedema coma. However, data from published literature support the intravenous use of levothyroxine sodium for the treatment of myxedema coma.

16 HOW SUPPLIED/STORAGE AND HANDLING

16.1 How Supplied

Levothyroxine Sodium for Injection is available in three dosage strengths.

Product Code | Unit of Sale | Strength | Reconstituted Concentration | Each
PA506107 | NDC 42023-201-01; Individually Packaged | 100 mcg per vial | 20 mcg per mL | NDC 42023-201-01; Vial
PA506247 | NDC 42023-202-01; Individually Packaged | 200 mcg per vial | 40 mcg per mL | NDC 42023-202-01; Vial
PA506248 | NDC 42023-203-01; Individually Packaged | 500 mcg per vial | 100 mcg per mL | NDC 42023-203-01; Vial

16.2 Storage and Handling

Protect from light and store dry product at 20° to 25°C (68° to 77°F) [see USP Controlled Room Temperature]. Reconstituted drug product is preservative free. Discard any unused portion.

The container closure is not made with natural rubber latex.
Manufactured for:

Endo USA

Malvern, PA 19355
451495A

OS201J-01-23-02

PACKAGE LABEL - PRINCIPAL DISPLAY - Levothyroxine 100 mcg Single Dose Vial Label

NDC 42023-201-01 PA506107
Levothyroxine Sodium For Injection

100 mcg per vial

For Intravenous Use

Single Dose Vial

Discard any unused portion.

Rx only

PACKAGE LABEL - PRINCIPAL DISPLAY - Levothyroxine 100 mcg Single Dose Vial Carton Panel

NDC 42023-201-01 PA506107

Levothyroxine Sodium For Injection

100 mcg per vial

For Intravenous Use

Single Dose Vial

Discard any unused portion.

Rx only

PACKAGE LABEL - PRINCIPAL DISPLAY - Levothyroxine 500 mcg Single Dose Vial Label

NDC 42023-203-01 PA506248

Levothyroxine Sodium For Injection

500 mcg per vial

For Intravenous Use

Single Dose Vial

Discard any unused portion.

Rx only

PACKAGE LABEL - PRINCIPAL DISPLAY - Levothyroxine 500 mcg Single Dose Vial Carton Panel

NDC 42023-203-01 PA506248

Levothyroxine Sodium For Injection

500 mcg per vial

For Intravenous Use

Single Dose Vial

Discard any unused portion.

Rx only

PACKAGE LABEL - PRINCIPAL DISPLAY - Levothyroxine 200 mcg Single Dose Vial Label

NDC 42023-202-01 PA506247

Levothyroxine Sodium For Injection

200 mcg per vial

For Intravenous Use

Single Dose Vial

Discard any unused portion.

Rx only

PACKAGE LABEL - PRINCIPAL DISPLAY - Levothyroxine 200 mcg Single Dose Vial Carton Label

NDC 42023-202-01 PA506247

Levothyroxine Sodium For Injection

200 mcg per vial

For Intravenous Use

Single Dose Vial

Discard any unused portion.

Rx only